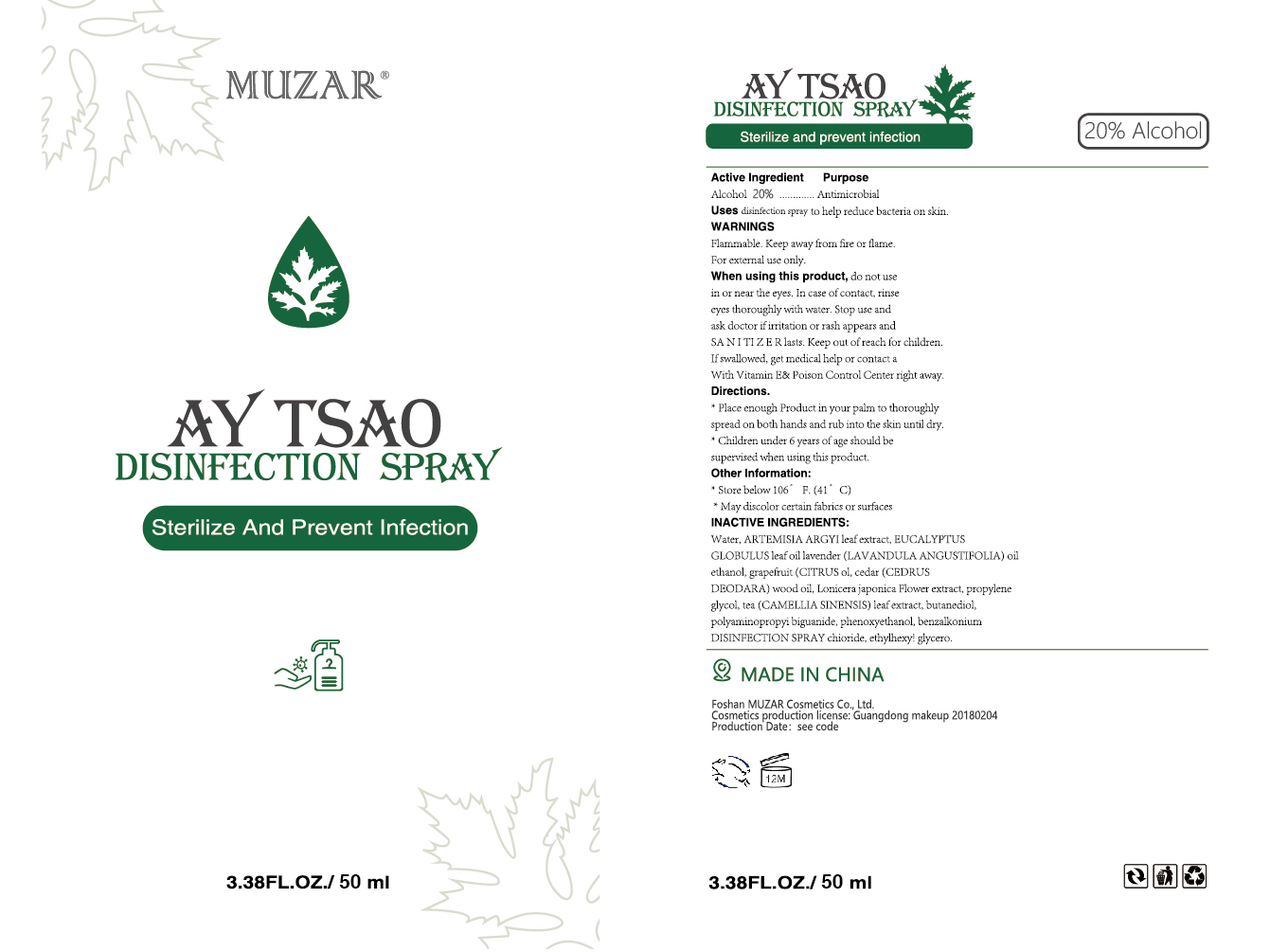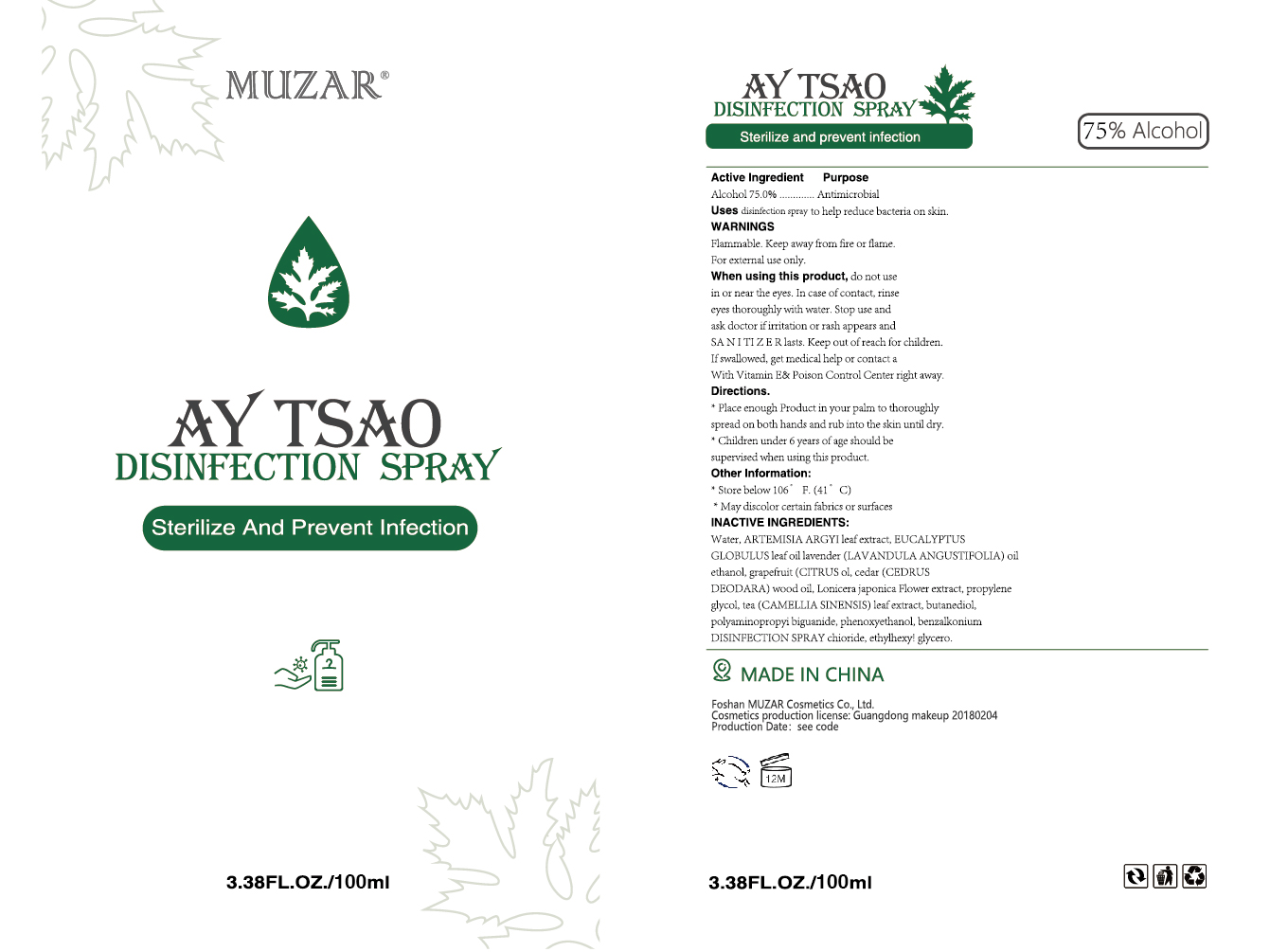 DRUG LABEL: D S
NDC: 74041-002 | Form: GEL
Manufacturer: Foshan MUZAR Cosmetics Co., Ltd
Category: otc | Type: HUMAN OTC DRUG LABEL
Date: 20200424

ACTIVE INGREDIENTS: ALCOHOL 20 mL/100 mL
INACTIVE INGREDIENTS: PROPYLENE GLYCOL; TEA LEAF; WATER; PHENOXYETHANOL; BUTANEDIOL (MIXED ISOMERS); ARTEMISIA ARGYI LEAF

DISINFECTION SPRAY

Active Ingredient

Alcohol 20%

Purpose

Antimicrobial

Uses

disinfection spray to help reduce bacteria on skin.

WARNINGS

Flammable.Keep away from fire or flame.For external use only.

When using this product

do not use in or near the eyes.In case of contact,rinse eyes thoroughly with water.Stop use and ask doctor if irritation or rash appears and SANITIZER lasts.Keep out of reach for children.If swallowed,get medical help or contact a With Vitamin E& Poison Control Center right away.

Directions

Place enough Product in your palm to thoroughly spread on both hands and rub into the skin until dry.

Children under 6 years of age should be supervised when using this product.

Other Information

Store below 106°F.(41°C)

May discolor certain fabrics or surfaces

INACTIVE INGREDIENTS

Water,ARTEMISIA ARGYI leaf extract, EUCALYPTUS GLOBULUS leaf oil lavender(LAVANDULA ANGUSTIFOLIA) oil

ethanol,grapefruit(CITRUS ol,cedar(CEDRUS DEODARA) wood oil,Lonicera japonica Flower extract, propylene glycol,tea(CAMELLIA SINENSIS) leaf extract, butanediol,polyaminopropyi biguanide, phenoxyethanol, benzalkonium DISINFECTION SPRAY chioride,

ethylhexy! glycero.